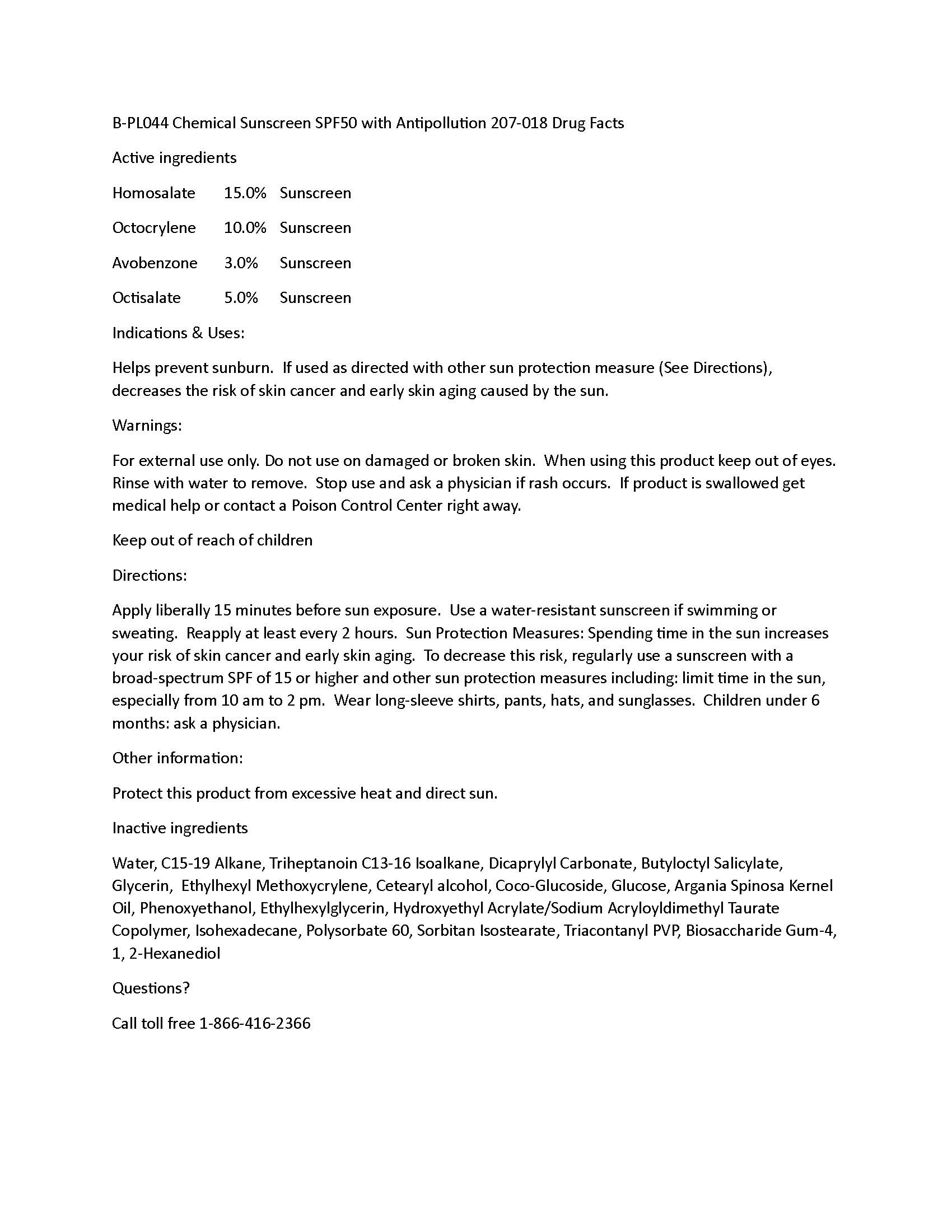 DRUG LABEL: Chemical Sunscreen SPF50 with Antipollution
NDC: 60232-4400 | Form: LOTION
Manufacturer: Swiss-American CDMO, LLC
Category: otc | Type: HUMAN OTC DRUG LABEL
Date: 20241018

ACTIVE INGREDIENTS: HOMOSALATE 150 g/1000 g; OCTOCRYLENE 100 g/1000 g; AVOBENZONE 30 g/1000 g; OCTISALATE 50 g/1000 g
INACTIVE INGREDIENTS: WATER; C15-19 ALKANE; TRIHEPTANOIN; DICAPRYLYL CARBONATE; BUTYLOCTYL SALICYLATE; GLYCERIN; COCO-GLUCOSIDE; ARGANIA SPINOSA SEED; PHENOXYETHANOL; ETHYLHEXYLGLYCERIN; HYDROXYETHYL ACRYLATE/SODIUM ACRYLOYLDIMETHYL TAURATE COPOLYMER (100000 MPA.S AT 1.5%); ISOHEXADECANE; POLYSORBATE 60; SORBITAN ISOSTEARATE; TRIACONTANYL PVP (WP-660); BIOSACCHARIDE GUM-4; 1,2-HEXANEDIOL; C13-16 ISOPARAFFIN; ETHYLHEXYL METHOXYCRYLENE; CETOSTEARYL ALCOHOL; ANHYDROUS DEXTROSE

Chemical Sunscreen SPF50 with Antipollution

Warnings

For external use only. Do not use on damaged or broken skin. When using this product keep out of eyes. Rinse with water to remove. Stop use and ask a physician if rash occurs. If product is swallowed get medical help or contact a Poison Control Center right away.

Indications and Uses

Helps prevent sunburn. If used as directed with other sun protection measure (See Directions), decreases the risk of skin cancer and early skin aging caused by the sun.

Purpose

Sunscreen

Active Ingredients

Homosalate 15.0% Sunscreen
Octocrylene 10.0% Sunscreen
Avobenzone 3.0% Sunscreen
Octisalate 5.0% Sunscreen

Keep out of reach of children

Directions

Apply liberally 15 minutes before sun exposure. Use a water-resistant sunscreen if swimming or sweating. Reapply at least every 2 hours. Sun Protection Measures: Spending time in the sun increases your risk of skin cancer and early skin aging. To decrease this risk, regularly use a sunscreen with a broad-spectrum SPF of 15 or higher and other sun protection measures including: limit time in the sun, especially from 10 am to 2 pm. Wear long-sleeve shirts, pants, hats, and sunglasses. Children under 6 months: ask a physician.

Other information:

Protect this product from excessive heat and direct sun.

Inactive Ingredients

Water, C15-19 Alkane, Triheptanoin C13-16 Isoalkane, Dicaprylyl Carbonate, Butyloctyl Salicylate, Glycerin, Ethylhexyl Methoxycrylene, Cetearyl alcohol, Coco-Glucoside, Glucose, Argania Spinosa Kernel Oil, Phenoxyethanol, Ethylhexylglycerin, Hydroxyethyl Acrylate/Sodium Acryloyldimethyl Taurate Copolymer, Isohexadecane, Polysorbate 60, Sorbitan Isostearate, Triacontanyl PVP, Biosaccharide Gum-4, 1,2-Hexanediol

Questions

Call toll free 1-866-416-2366